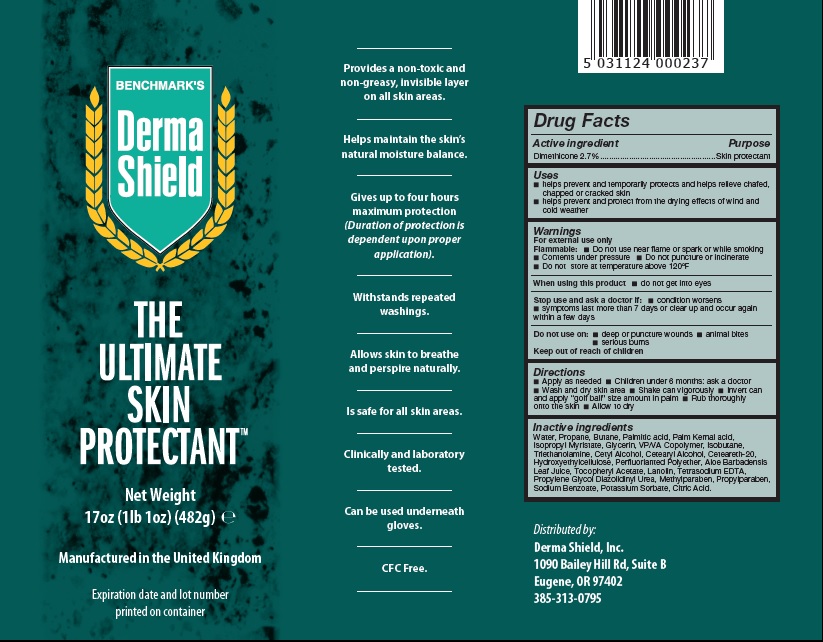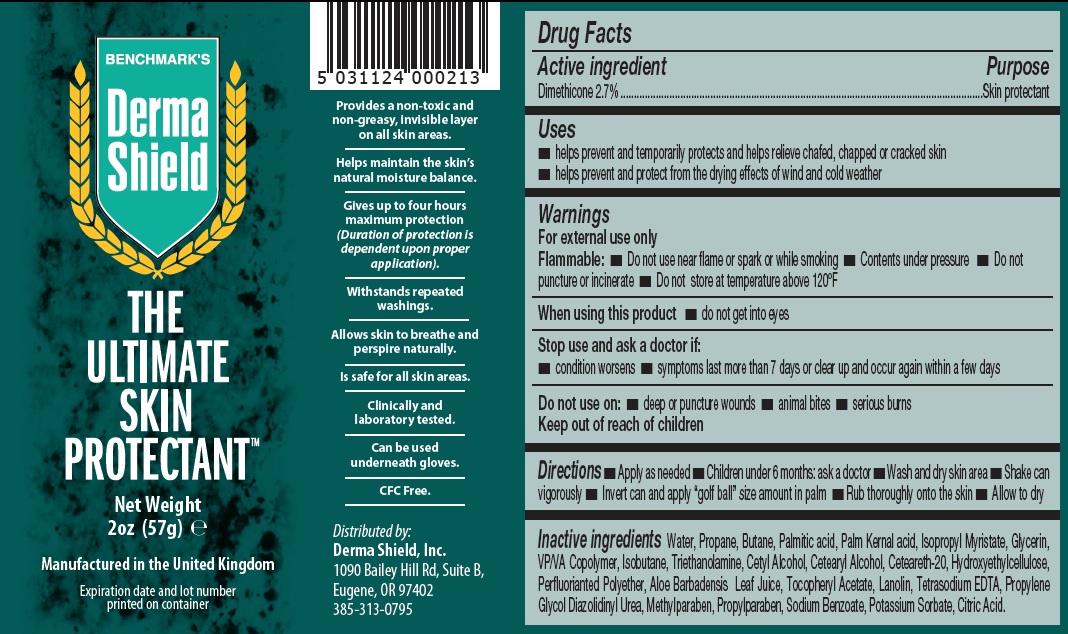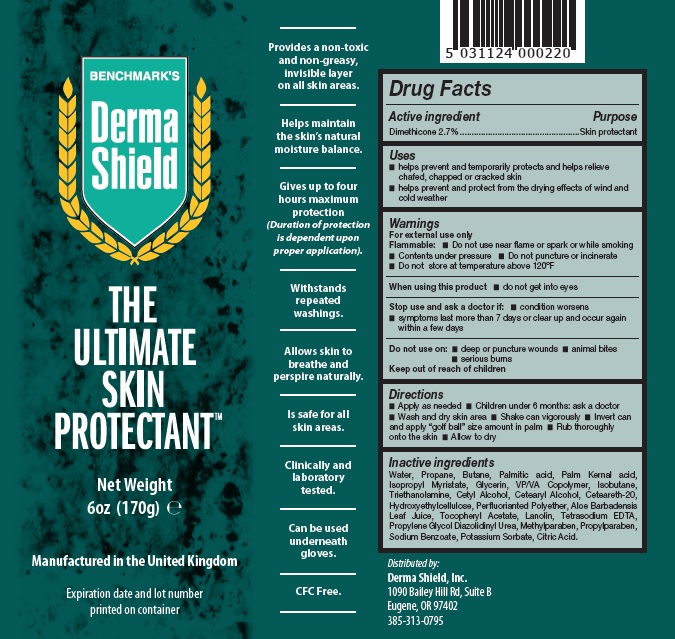 DRUG LABEL: Benchmarks Derma Shield
NDC: 80905-001 | Form: AEROSOL
Manufacturer: STAR COLOUR LABORATORIES
Category: otc | Type: HUMAN OTC DRUG LABEL
Date: 20201009

ACTIVE INGREDIENTS: DIMETHICONE 2.7 g/100 g
INACTIVE INGREDIENTS: LANOLIN; PROPYLPARABEN; POLYOXYL 20 CETOSTEARYL ETHER; CITRIC ACID MONOHYDRATE; DIAZOLIDINYL UREA; GLYCERIN; HYDROXYETHYL CELLULOSE (4000 MPA.S AT 1%); METHYLPARABEN; PALM KERNEL ACID; PROPYLENE GLYCOL; SODIUM BENZOATE; COPOVIDONE K25-31; EDETATE SODIUM; .ALPHA.-TOCOPHEROL ACETATE; TROLAMINE; ALOE VERA LEAF; WATER; CETYL ALCOHOL; ISOBUTANE; ISOPROPYL MYRISTATE; PALMITIC ACID; PERFLUOROPOLYMETHYLISOPROPYL ETHER; POTASSIUM SORBATE; PROPANE; BUTANE

Active Ingredient(s)

Dimethicone, 2.7%

Uses

- Helps prevent and temporarily protects and helps relieve chafed, chapped or cracked skin
- Helps prevent and protect from the drying effects of wind and cold weather

Purpose

Skin protectant

Warnings

For external use only

Flammable:

- Do not use near flame or spark or while smoking
- Contents under pressure
- Do not puncture or incinerate
- Do not store at temperature above 120oF

Do not use on:

- deep or puncture wounds
- animal bites
- serious burns
- keep out of reach of children

Directions

- Apply as needed
- Children under 6 months: ask a doctor
- Wash and dry skin area
- Shake can vigorously
- Invert can and apply "golf ball" sized amount in palm
- Rub thoroughly onto the skin
- Allow to dry

Inactive ingredients

Water, Propane, Butane, Palmitic acid, Palm Kernal acid, Isopropyl Myrisate, Glycerin, VP/VA Copolymer, Isobutane, Triethanolamine, Cetyl Alcohol, Cetearyl Alcohol, Ceteareth-20, Hydroxyethylcellulose, Perfluorianted Polyether, Aloe Barbadensis Leaf Juice, Tocopheryl Acetate, Lanolin, Tetrasodium EDTA, Propylene Glycol Diazolindinyl Urea, Methylparaben, Propylparaben, Sodium Benzoate, Potassium Sorbate, Citric Acid

PACKAGE LABEL.PRINCIPAL DISPLAY PANEL

Derma Shield 2oz Aerosol USA

Derma Shield 6oz Aerosol USA

Derma Shield 17oz Aerosol USA